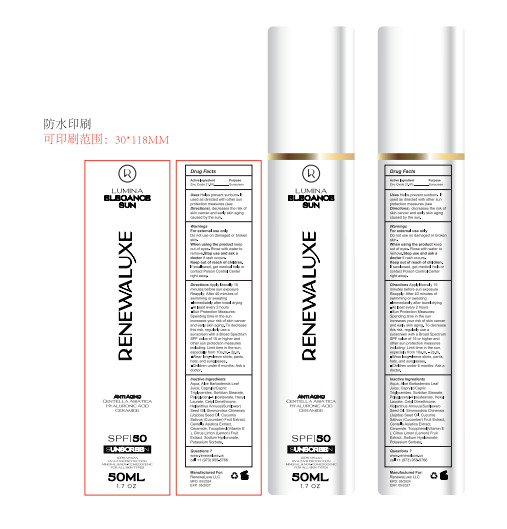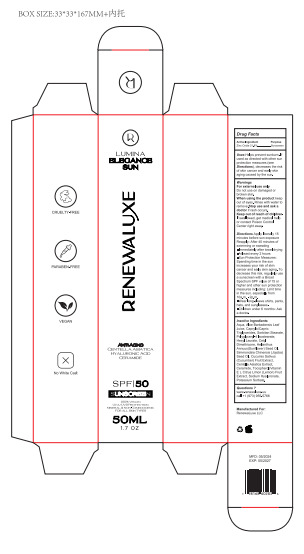 DRUG LABEL: RENEWALUXE SPF 50 Sunscreen
NDC: 83447-005 | Form: CREAM
Manufacturer: Guangzhou Fantesy Biotechnology Co.,Ltd
Category: otc | Type: HUMAN OTC DRUG LABEL
Date: 20260106

ACTIVE INGREDIENTS: ZINC OXIDE 21.8 g/100 mL
INACTIVE INGREDIENTS: SORBITAN MONOSTEARATE; POLYGLYCERYL-4 ISOSTEARATE; HEXYL LAURATE; COCONUT OIL; JOJOBA OIL; CENTELLA ASIATICA TRITERPENOIDS; CERAMIDE 9; TOCOPHEROL; LEMON; HYALURONATE SODIUM; POTASSIUM SORBATE; ALOE VERA LEAF; WATER; CETYL DIMETHICONE 45; MEDIUM-CHAIN TRIGLYCERIDES

83447-005

ACTIVE INGREDIENT

Zinc Oxide 21.8%

PURPOSE

sunscreen

Uses

Uses Helps prevent sunburn. If used as directed with other sun
protection measures (see Directions), decreases the risk of
skin cancer and early skin aging caused by the sun.

Warnings

For external use only
Do not use on damaged or broken skin.
When using the product keep out of eyes. Rinse with water to remove.Stop use and ask a doctor if rash occurs.

Keep out of reach of children. If swallowed, get medical help or contact Poison Control Center right away.

Do not use on damaged or broken skin.

Keep out of reach of children.
If swallowed, get medical help or
contact Poison Control Center
right away.

Directions

Directions Apply liberally 15 minutes before sun exposure Reapply: After 40 minutes of
swimming or sweating
■Immediately after towel drying
■At least every 2 hours
■Sun Protection Measures: Spending time in the sun increases your risk of skin cancer
and early skin aging. To decrease this risk, regularly use a sunscreen with a Broad Spectrum

SPF value of 15 or higher and other sun protection measures including: Limit time in the sun,
especially from 10a.m. - 2p.m.
■Wear long-sleeve shirts, pants, hats, and sunglasses.
■Children under 6 months: Ask a doctor.

Other information

Protect the product in this container from excessive heat and direct sun